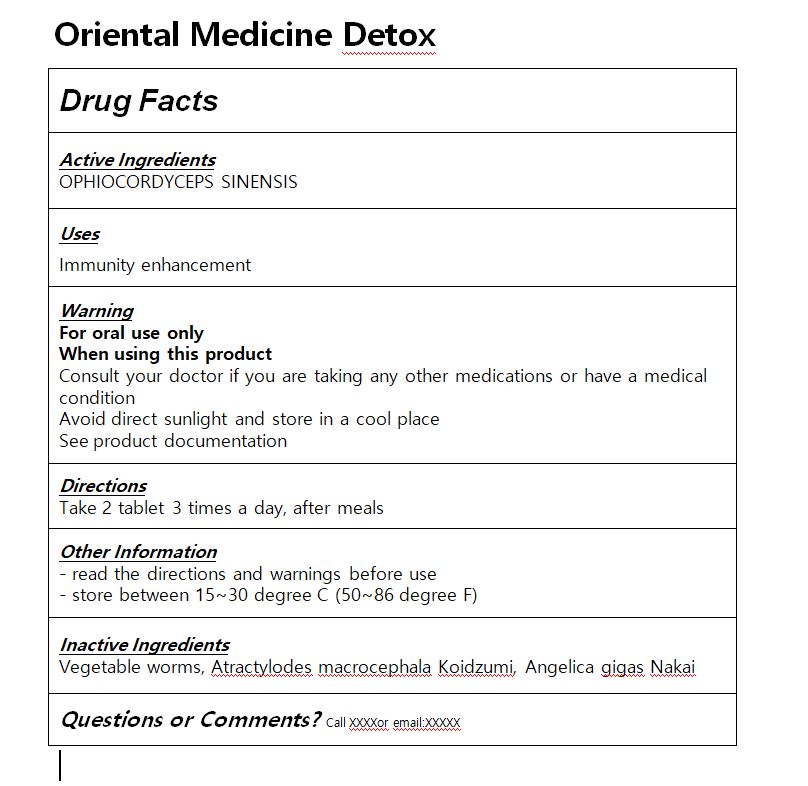 DRUG LABEL: HempSeed Cordyceps
NDC: 83036-0001 | Form: CAPSULE
Manufacturer: Tong Cheon Dang
Category: otc | Type: HUMAN OTC DRUG LABEL
Date: 20221004

ACTIVE INGREDIENTS: OPHIOCORDYCEPS SINENSIS 0.1 g/1 1
INACTIVE INGREDIENTS: ANGELICA GIGAS WHOLE

ACTIVE INGREDIENT

OPHIOCORDYCEPS SINENSIS

INACTIVE INGREDIENT

Vegetable worms, Atractylodes macrocephala Koidzumi, Angelica gigas Nakai

PURPOSE

Immunity enhancement

keep out of reach of the children

INDICATIONS AND USAGE

Take 2 tablet 3 times a day, after meals

WARNINGS

Consult your doctor if you are taking any other medications or have a medical condition
Avoid direct sunlight and store in a cool place
See product documentation

DOSAGE AND ADMINISTRATION

for oral use only